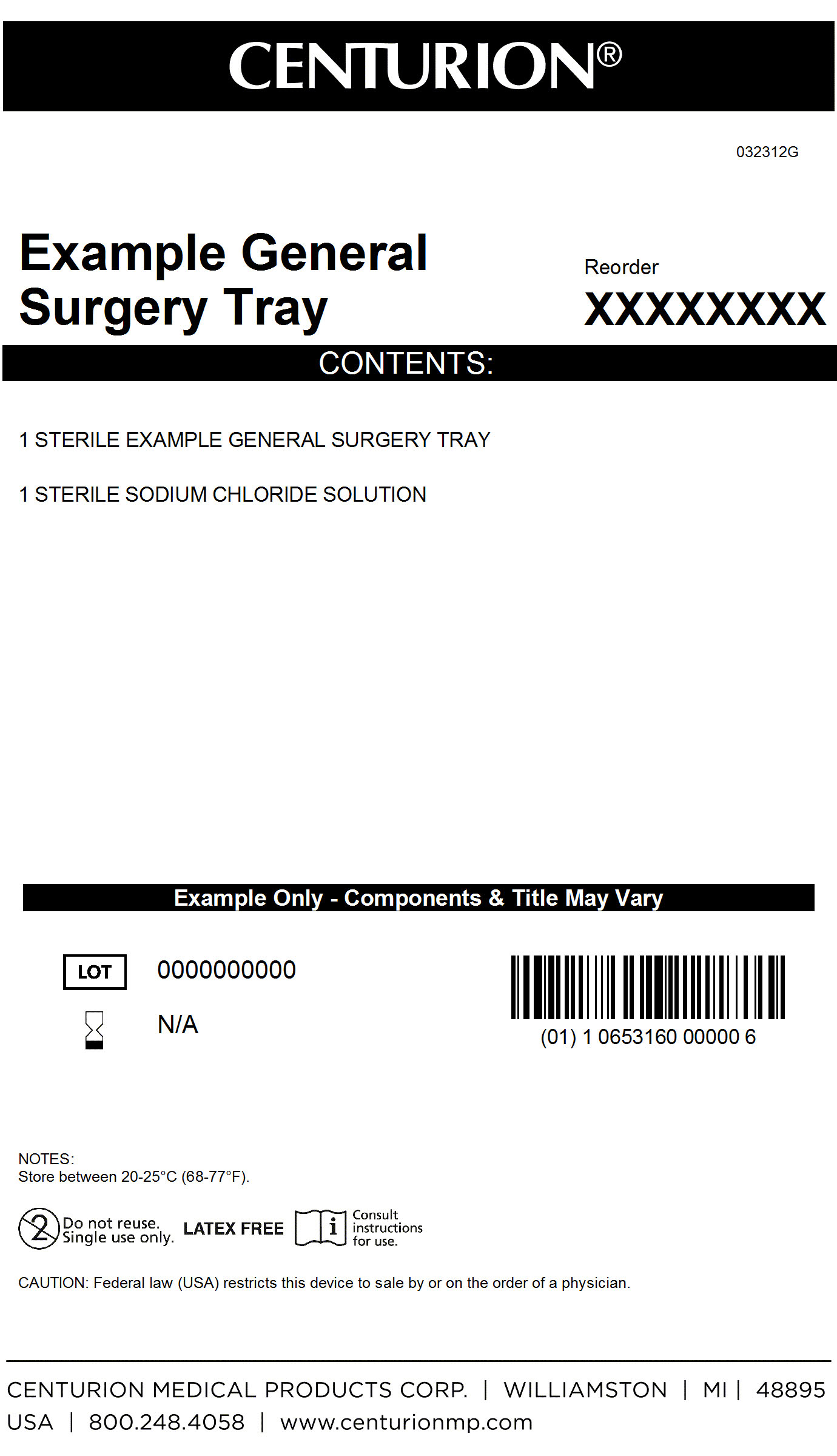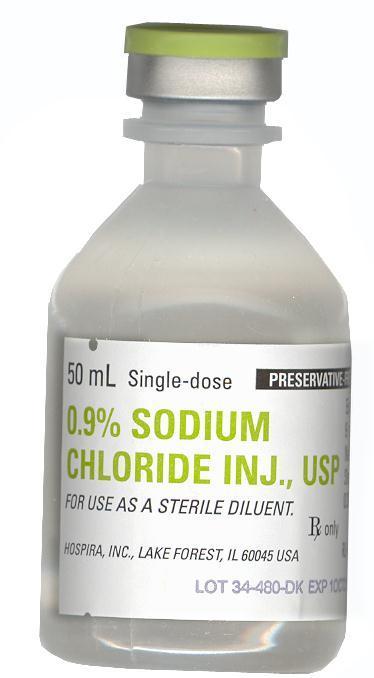 DRUG LABEL: General Surgery Kit
NDC: 24840-1536 | Form: KIT | Route: INTRAVENOUS
Manufacturer: Centurion Medical Products
Category: other | Type: MEDICAL DEVICE
Date: 20120927

ACTIVE INGREDIENTS: SODIUM CHLORIDE 9 mg/1 mL
INACTIVE INGREDIENTS: WATER; HYDROCHLORIC ACID; SODIUM HYDROXIDE

General Surgery Kit

DESCRIPTION

This preparation is designed solely for parenteral use only after addition of drugs that require dilution or must be dissolved in an aqueous vehicle prior to injection. 0.9% Sodium Chloride Injection, USP is a sterile, nonpyrogenic, istonic solution of sodium chloride and water for injection. It contains no bacteriostat, antimicrobial agent or added buffer and is supplied only in single dose containters to dilute or dissolve drugs for injection. Sodium Chloride is chemically designated as NaCl, a white crystalline compound freely soluable in water. The solution may contain hydrochloric acid and/or sodium hydroxide for pH adjustment. pH 5.3 (4.5 to 7.0).

PACKAGE LABEL

MM